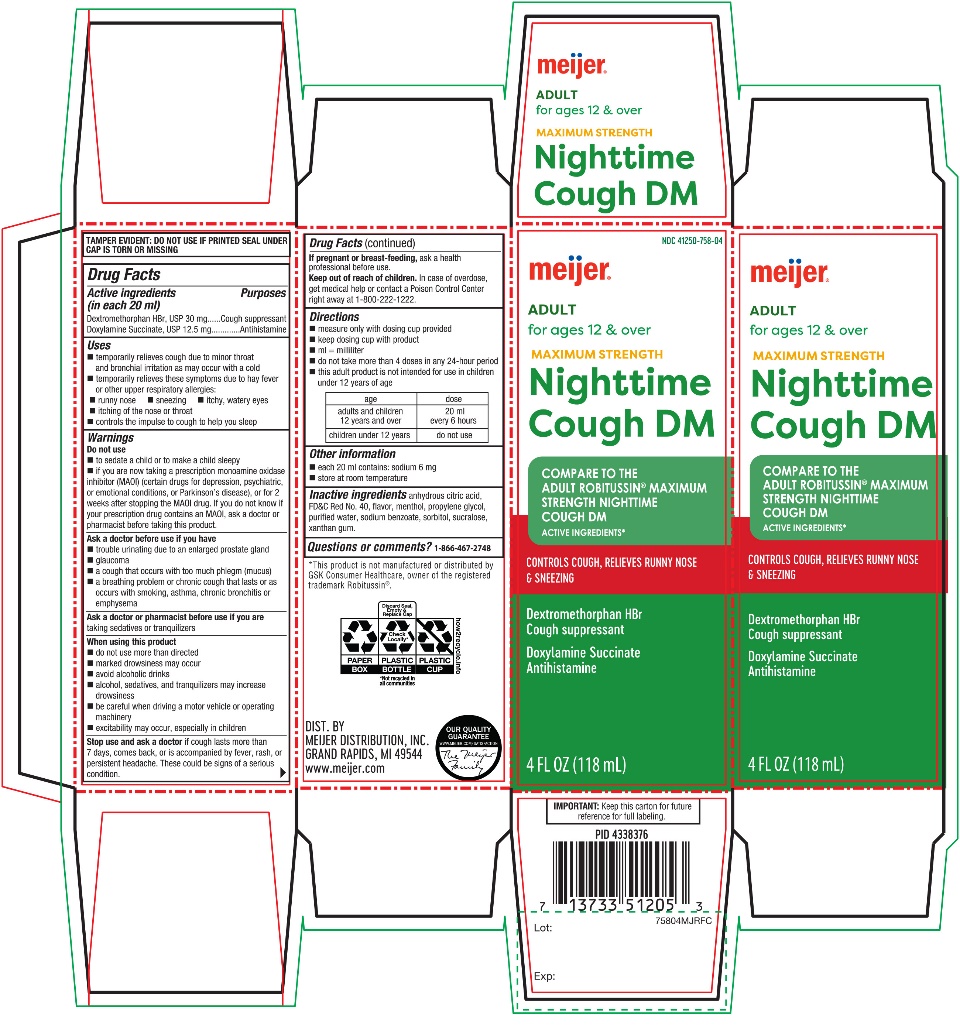 DRUG LABEL: meijer Maximum Strength Nighttime Cough DM
NDC: 41250-758 | Form: SOLUTION
Manufacturer: MEIJER DISTRIBUTION INC
Category: otc | Type: HUMAN OTC DRUG LABEL
Date: 20251024

ACTIVE INGREDIENTS: DEXTROMETHORPHAN HYDROBROMIDE 30 mg/20 mL; DOXYLAMINE SUCCINATE 12.5 mg/20 mL
INACTIVE INGREDIENTS: ANHYDROUS CITRIC ACID; FD&C RED NO. 40; MENTHOL, UNSPECIFIED FORM; PROPYLENE GLYCOL; WATER; SODIUM BENZOATE; SORBITOL; SUCRALOSE; XANTHAN GUM

Meijer®Maximum Strength Nighttime Cough DM

Drug Facts

ACTIVE INGREDIENT

PURPOSE

Active ingredients (in each 20 ml) | Purposes
Dextromethorphan HBr, USP 30 mg | Cough suppressant
Doxylamine Succinate, USP 12.5 mg | Antihistamine

Uses

- temporarily relieves cough due to minor throat and bronchial irritation as may occur with a cold
- temporarily relieves these symptoms due to hay fever or other upper respiratory allergies:
  - runny nose
  - sneezing
  - itchy, watery eyes
  - itching of the nose or throat
- controls the impulse to cough to help you sleep

Warnings

Do not use

- to sedate a child or to make a child sleepy
- if you are now taking a prescription monoamine oxidase inhibitor (MAOI) (certain drugs for depression, psychiatric, or emotional conditions, or Parkinson's disease), or for 2 weeks after stopping the MAOI drug. If you do not know if your prescription drug contains an MAOI, ask a doctor or pharmacist before taking this product.

Ask a doctor before use if you have

- trouble urinating due to an enlarged prostate gland
- glaucoma
- a cough that occurs with too much phlegm (mucus)
- a breathing problem or chronic cough that lasts or as occurs with smoking, asthma, chronic bronchitis or emphysema

Ask a doctor or pharmacist before use if you aretaking sedatives or tranquilizers

When using this product

- do not use more than directed
- marked drowsiness may occur
- avoid alcoholic drinks
- alcohol, sedatives, and tranquilizers may increase drowsiness
- be careful when driving a motor vehicle or operating machinery
- excitability may occur, especially in children

Stop use and ask a doctor ifcough lasts more than 7 days, comes back, or is accompanied by fever, rash, or persistent headache. These could be signs of a serious condition.

PREGNANCY OR BREAST FEEDING

If pregnant or breast-feeding,ask a health professional before use.

Keep out of reach of children.In case of overdose, get medical help or contact a Poison Control Center right away at 1-800-222-1222.

Directions

- measure only with dosing cup provided
- keep dosing cup with product
- mL = milliliter
- do not take more than 4 doses in any 24-hour period
- this adult product is not intended for use in children under 12 years of age

age | dose
adults and children 12 years and over | 20 ml every 6 hours
children under 12 years | do not use

Other information

- each 20 ml contains: sodium 14 mg
- store at room temperature.

Inactive ingredients

anhydrous citric acid, FD&C Red #40, flavor, menthol, propylene glycol, purified water, sodium benzoate, sorbitol, sucralose, xanthan gum.

Questions or comments?

1-866-467-2748

PRINCIPAL DISPLAY PANEL

meijer®

NDC 41250-758-04

Compare to Robitussin®Maximum Strength Nighttime Cough DM active ingredient*

For Ages 12 & Over

adult nighttime cough DM

DEXTROMETHORPHAN HBr 30mg/20mL (Cough Suppressant)
DOXYLAMINE SUCCINATE 12.5mg/20mL (Antihistamine)

MAXIMUM STRENGTH

Nighttime

RELIEF OF: Cough, Itchy Throat, Runny Nose

4 FL OZ (118 mL)

*This product is not manufactured or distributed by Pfizer Inc, distributor of Robitussin.®

Maximum Strength claim based on maximum levels of active ingredient per dose.

DIST. BY MEIJER DISTRIBUTION, INC.

GRAND RAPIDS, MI 49544

www.meijer.com

MEIJER PHARAMACISTS RECOMMENDED

MONEY BACK GUARANTEE